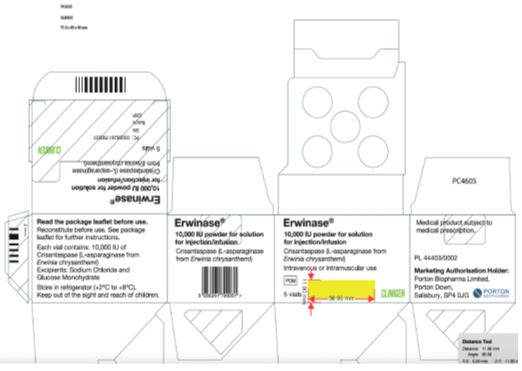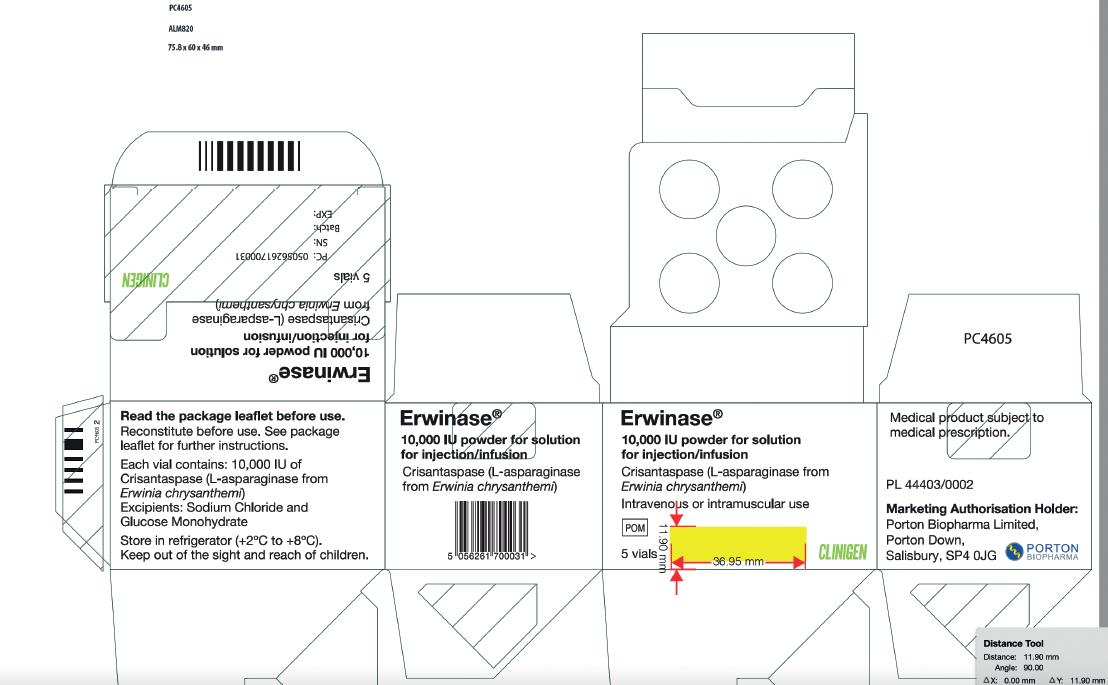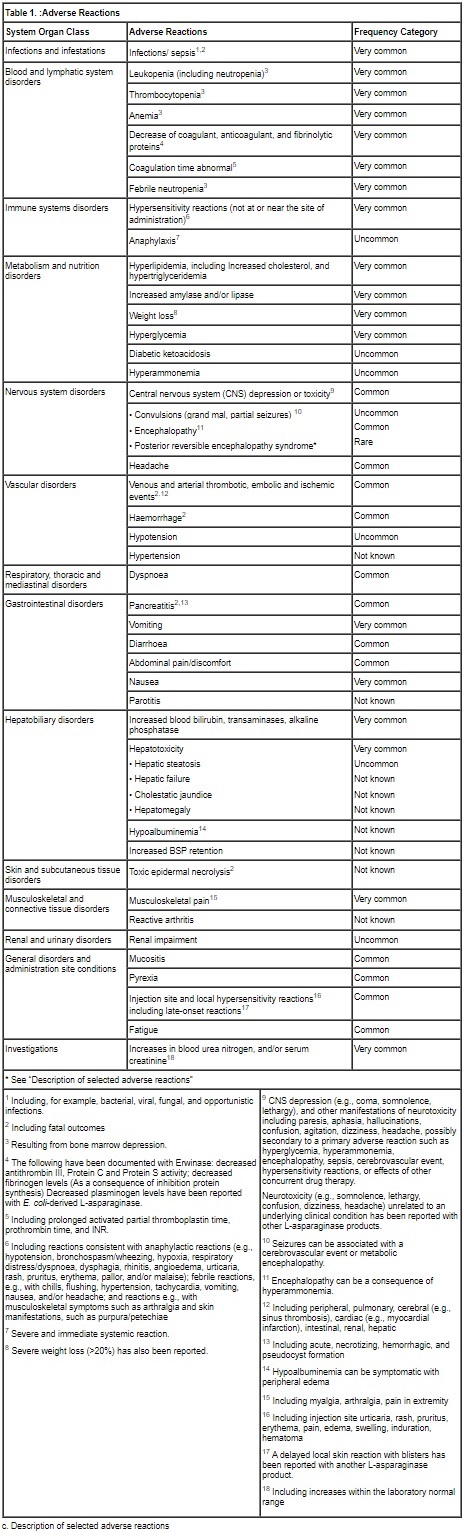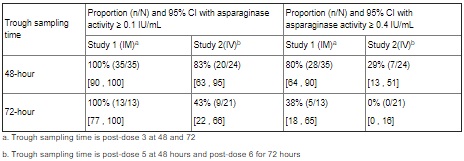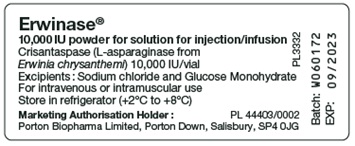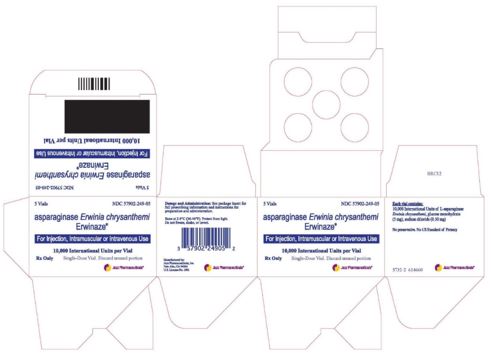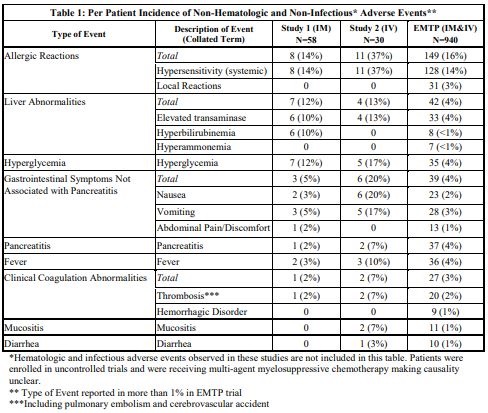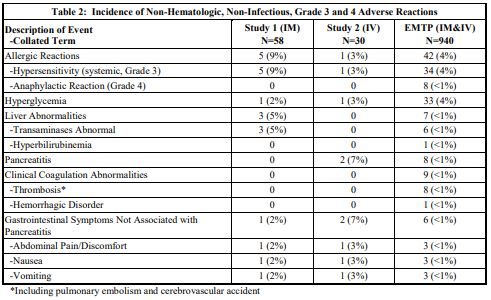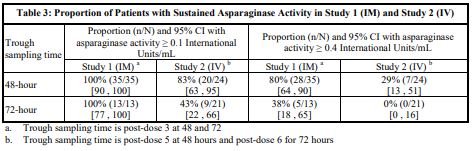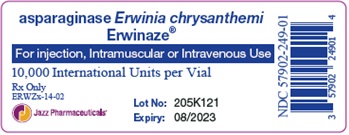 DRUG LABEL: ERWINASE
NDC: 81561-413 | Form: INJECTION, POWDER, LYOPHILIZED, FOR SOLUTION
Manufacturer: Porton Biopharma Limited
Category: prescription | Type: HUMAN PRESCRIPTION DRUG LABEL
Date: 20210615

ACTIVE INGREDIENTS: ASPARAGINASE ERWINIA CHRYSANTHEMI 10000 [iU]/1 mL
INACTIVE INGREDIENTS: DEXTROSE MONOHYDRATE 5 mg/1 mL; SODIUM CHLORIDE 0.5 mg/1 mL

HEALTH CARE PROVIDER LETTER

25 May 2021

IMPORTANT PRESCRIBING INFORMATION

Subject: Temporary importation of Erwinase® (crisantaspase) injection, powder, lyophilized, for solution to address a drug shortage in the United States (U.S.)

Dear Healthcare Professional,

In order to alleviate a critical shortage of U.S.-licensed asparaginase erwinia chrysanthemi injection, powder, lyophilized, for solution in the US market, Porton Biopharma Limited (PBL) is coordinating with the U.S. Food and Drug Administration (FDA) to make available in the U.S. the non-FDA licensed Erwinase (crisantaspase) 10,000 IU/vial powder for solution for injection/infusion.

At this time, no other entity except PBL (via its distributor Clinigen Inc.) is authorized by the FDA to import and distribute Erwinase in the U.S. However, this does not represent a formal FDA approval of Erwinase in the U.S.

Effective immediately, PBL (via its distributor Clinigen Inc.) will distribute the following presentation of Erwinase (Batch number: W060172) to address the critical shortage:

Product Name | Pack Size | Description | U.K. Marketing Authorization Number | NDC
Erwinase, 10,000 IU/vial, Powder for solution for injection/infusion. | 5 vials | Powder for solution for injection/infusion. White lyophilised powder in a vial. | PL 44403/0002 | NDC 81561-413-05*

*This NDC code has been assigned by PBL. The code is presented on the carton. It should be noted that the importer and distributor in the U.S. will be Clinigen Inc. The same NDC code will be used throughout the distribution chain of the product in the U.S.

It is important to note the following:

- Erwinase is available in the U.S. only by prescription.
- There is no barcode on this product for use with U.S. barcode scanning systems.
  Alternative procedures should be followed to assure that the correct drug product is being used and administered to individual patients.
- Contraindications to use of Erwinase include:
  - Serious hypersensitivity reactions to asparaginase erwinia chrysanthemi, including anaphylaxis
  - Serious pancreatitis with any prior asparaginase therapy
  - Serious thrombosis with any prior asparaginase therapy
  - Serious hemorrhagic events with any prior asparaginase therapy
- There are differences between the U.S.-licensed asparaginase erwinia chrysanthemi Prescribing Information and the Erwinase Summary of Product Characteristics (Appendix 2). Use the recommended dosage for U.S.-licensed asparaginase erwinia chrysanthemi
  - To substitute for each planned dose of pegaspargase, the recommended dosage of Erwinase is 25,000 International Units/m^2 administered intramuscularly or intravenously three times a week (Monday/Wednesday/Friday) for two consecutive weeks (total six doses).
  - When administering Erwinase intravenously, the desired NSAA levels may not be achieved; consider monitoring nadir (pre-dose) serum asparaginase activity (NSAA) levels and switching to intramuscular administration if desired NSAA levels are not achieved with intravenous dosing.
- There are differences between the U.S.-licensed product and Erwinase in the Preparation and Handling Instructions (Appendix 2). Use the recommended handling instruction for U.S.-licensed asparaginase erwinia chrysanthemi.
  - Do not freeze or refrigerate reconstituted solution and administer within 4 hours or discard.
- There are differences between the U.S.-licensed product and Erwinase in the format and content of the container and carton labelling.
  - The Erwinase carton includes an insert providing both the U.K. prescribing information (Summary of Product Characteristics) and information for the patient (package leaflet). See the bullet above regarding the recommended dosage instructions for Erwinase.
  - The vial label will display the text used and approved for marketing the product in U.K. Please see the product comparison tables at the end of this letter (Appendix 1).
  - The packaging of Erwinase does not include serialization information and does not meet the product identifier requirements of section 582(b)(2) of the Federal Food, Drug and Cosmetic Act.

Ensure that your staff and others in your office and/or pharmacy who may be involved in the prescribing and/or dispensing of Erwinase- asparaginase injection, powder, lyophilized, for solution receive a copy of this letter, review the information and instruct patients on the differences between Erwinase and U.S.-licensed asparaginase erwinia chrysanthemi.

This letter and the attachments are not intended as a complete description of the benefits and risks related to the use of Erwinase. See the full prescribing information on the UK MHRA website at https://products.mhra.gov.uk/product/?product=ERWINASE%2010%20000%20UNITS%2FVIAL%20%20LYOPHILISATE%20FOR%20SOLUTION%20FOR%20INJECTION

Contact Information:

If you have any questions about the information contained in this letter, any quality related problems, or questions on the use of Erwinase, please contact Porton Biopharma Limited via email medinfo@portonbiopharma.com or contact directly at 1-855-209-2652.

To place an order, contact McKesson Plasma and Biologics (MPB) directly at 1-877-625-2566.

Adverse Events and Product Quality Complaints:

Report adverse events associated with the use of Erwinase to drugsafety@portonbiopharma.com via email or contact directly at 1-855-209-2652.

Adverse events, medication errors or quality problems experienced with the use of Erwinase may also be reported to the FDA’s MedWatch Adverse Event Reporting Program either online, regular mail, or by fax:

- Complete and submit the report Online: www.fda.gov/medwatch/report.htm
- Regular Mail or Fax: Download form www.fda.gov/medwatch/getforms.htm or call 1-800-332-1088 to request a reporting form, then complete and return to the address on the pre-addressed form, or submit by fax to 1-800-FDA-0178 (1-800-332-0178).

We remain at your disposal to answer any questions you may have about our product and to provide more information if needed.

Yours sincerely,

Dr. Elizabeth Madichie | Dr. Henno Welgemoed
Director of Regulatory Affairs & Pharmacovigilance | Director of Medical Affairs
Porton Biopharma Limited, U.K. | Clinigen Group plc, U.K.

Enclosures:

Appendix 1 – Product Label and Product Characteristics Side-by-Side Comparison Table

Appendix 2 – Prescribing Information Side-by-Side Comparison Table

Appendix 1 – Product Label and Product Characteristics Side-by-Side Comparison Table

 | U.S. FDA Licensed Product | Imported Product
Product Name | Erwinaze®- asparaginase injection, powder, lyophilized, for solution | Erwinase® 10,000 IU/vial Powder for solution for injection/infusion
Strength | 10,000 International Units in a single-dose vial | 10,000 IU/vial
Carton Label Image
Vial Label Image
Route of Administration | Erwinaze can be administered intramuscularly or intravenously. | Erwinase solution can be given by intravenous infusion or intramuscular injection.
Ingredients | Erwinaze is supplied as a sterile, lyophilized, white powder in vials. Each vial contains 10,000 International Units of asparaginase Erwinia chrysanthemi, and the following inactive ingredients: glucose monohydrate (5.0 mg), sodium chloride (0.5 mg). | Crisantaspase (L-asparaginase from Erwinia chrysanthemi), 10,000 International units/vial.; List of excipients; Sodium Chloride; Glucose Monohydrate
Storage Conditions | Store unused or unopened vials and cartons at 36°F to 46°F (2°C to 8°C). Protect from light. Do not use Erwinaze after the expiration date on the vial. | Store in a refrigerator (+2°C to +8°C).

Appendix 2 – Prescribing Information Side-by-Side Comparison Table

A side-by-side comparison of the Erwinaze U.S. Prescribing Information (USPI) and Erwinase U.K. Summary of Product Characteristics (SmPC) is provided below. It is important to note that there are no significant differences in the indications, dosage and administration between the two products.

Side-by-Side Comparison Table:

 | U.S. FDA Licensed Product | Imported Product
Product name | Erwinaze®- asparaginase injection, powder, lyophilized, for solution | Erwinase® 10,000 IU/vial Powder for solution for injection/infusion
Indication | 1 Indications and Usage; ERWINAZE is indicated as a component of a multi-agent chemotherapeutic regimen for the treatment of patients with acute lymphoblastic leukemia (ALL) who have developed hypersensitivity to E. coli derived asparaginase. | 4 Clinical Particulars; 4.1 Therapeutic indications; Erwinase is indicated as a component of a chemotherapeutic regimen for the treatment of patients with acute lymphoblastic leukaemia (ALL) who have developed hypersensitivity to E. coli-derived asparaginase.; Erwinase is indicated in paediatric patients from the age of 4 months and in adults.
Dosage and administration | 2 Dosage and administration; 2.1 Recommended Dosage; To substitute for a dose of pegaspargase:; The recommended dose for each planned dose of pegaspargase is 25,000 International Units/m^2 administered intramuscularly or intravenously three times a week (Monday/Wednesday/Friday) for six doses.; To substitute for a dose of native E. coli asparaginase:; The recommended dose is 25,000 International Units/m^2 administered intramuscularly or intravenously for each scheduled dose of native E. coli asparaginase within a treatment.; When administering ERWINAZE intravenously, consider monitoring nadir (pre-dose) serum asparaginase activity (NSAA) levels and switching to intramuscular administration if desired NSAA levels are not achieved [see Clinical Pharmacology (12.3)]. | 4.2 Posology and method of administration; Posology; The recommended dosage is 20,000 or 25,000 IU/m^2 body surface area administered three times a week (e.g., Monday/Wednesday/Friday).; Therapy should be adjusted according to local treatment protocols.
 | 2.2 Preparation and Handling Instructions; - Visually inspect the ERWINAZE powder for foreign particulate matter and discoloration prior to reconstitution. Discard vial if present. - Reconstitute the contents of each vial by slowly injecting 1 or 2 mL of preservative free sterile sodium chloride (0.9%) injection (USP) against the inner vial wall. - Do not forcefully inject solution for reconstitution directly onto or into the powder. When reconstituted with 1 mL the resultant concentration is 10,000 International Units per mL. When reconstituted with 2 mL the resultant concentration is 5,000 International Units per mL. - Dissolve contents by gentle mixing or swirling. Do not shake or invert vial. - When reconstituted, ERWINAZE should be a clear, colorless solution. Inspect the solution after reconstitution and discard if any visible particles or protein aggregates are present. | 6.6 Special precautions for disposal and other handling; The contents of each vial should be reconstituted in 1 mL to 2 mL of sodium chloride (0.9%) solution for injection.; When reconstituted with 1 mL the resultant concentration is 10,000 IU/mL. When reconstituted with 2 mL the resultant concentration is 5,000 IU/mL; Slowly add the sodium chloride (0.9%) solution for injection. against the inner vial wall, do not squirt directly onto or into the powder.; Allow the contents to dissolve by gentle mixing or swirling maintaining the vial in an upright position, avoiding contact of the solution with the stopper. Avoid froth formation due to excessive or vigorous shaking.; The solution should be clear without any visible particles. Fine crystalline or thread-like wisps of protein aggregates may be visible if shaking is excessive. If there are any visible particles or protein aggregates present the reconstituted solution should be rejected.
 | - Calculate the dose needed and the volume needed to obtain the calculated dose. - Withdraw the volume containing the calculated dose from the vial into a polypropylene syringe within 15 minutes of reconstitution. For intravenous use, slowly inject the reconstituted ERWINAZE into an IV infusion bag containing 100 mL of normal saline acclimatized to room temperature. Do not shake or squeeze the IV bag. - If partial vial is used, do not save or reuse the unused drug for later administration. Discard unused portions. - Do not freeze or refrigerate reconstituted solution and administer within 4 hours or discard [see How Supplied/Storage and Handling (16)]. | Erwinase is not a cytotoxic medicinal product (such as vincristine or methotrexate) and does not require the special precautions needed for manipulating such agents. It should be handled in the same way as other therapeutic enzymes such as hyaluronidase.; The solution should be administered within 15 minutes of reconstitution. If a delay of more than 15 minutes between reconstitution and administration is unavoidable, the solution should be withdrawn into a glass or polypropylene syringe for the period of the delay.; Any unused product or waste material should be disposed of in accordance with local requirements.; The solution should be used within 8 hours.
 | 2.3 Administration Instructions; Administer ERWINAZE in a setting with resuscitation equipment and other agents necessary to treat anaphylaxis.; ERWINAZE solution can be administered by intramuscular injection or by intravenous infusion.; - For intramuscular use, limit the volume of reconstituted ERWINAZE at a single injection site to 2 mL; if reconstituted dose to be administered is greater than 2 mL, use multiple injection sites. - For intravenous use, infuse ERWINAZE in 100 mL of normal saline over 1 to 2 hours. Do not infuse other intravenous drugs through the same intravenous line while infusing ERWINAZE. | Method of administration; Erwinase solution can be given by intravenous infusion or intramuscular injection.; For IM injection the volume of reconstituted solution administered at a single injection site should not exceed 2 mL. Multiple injection sites should be used if this volume is exceeded.; For IV infusion, the reconstituted solution should be further diluted in 100 mL of normal saline and administered over 1 to 2 hours.; For further instructions on reconstitution of the medicinal product before administration, see section 6.6.
Description | 3 DOSAGE FORMS AND STRENGTHS; For injection: 10,000 International Units as a lyophilized powder in a single-dose vial for reconstitution; 11 DESCRIPTION; ERWINAZE (asparaginase Erwinia chrysanthemi) contains an asparagine specific enzyme derived from Erwinia chrysanthemi. L-asparaginase is a tetrameric enzyme consisting of four identical subunits, each having a molecular weight of about 35 kDa. The activity of ERWINAZE is expressed in terms of International Units.; ERWINAZE is supplied as a sterile, lyophilized, white powder in vials. Each vial contains 10,000 International Units of asparaginase Erwinia chrysanthemi, and the following inactive ingredients: glucose monohydrate (5.0 mg), sodium chloride (0.5 mg). | 2 QUALITATIVE AND QUANTITATIVE COMPOSITION; Crisantaspase (L-asparaginase from Erwinia chrysanthemi), 10,000 International units/vial.; For a full list of excipients, see section 6.1.; 3. PHARMACEUTICAL FORM; Powder for solution for injection/infusion.; White lyophilised powder in a vial.; 6.1 List of excipients; Sodium Chloride (0.5 mg); Glucose Monohydrate (5.0 mg)
Contraindications | 4 CONTRAINDICATIONS; ERWINAZE is contraindicated in patients with a history of:; - Serious hypersensitivity reactions to ERWINAZE, including anaphylaxis - Serious pancreatitis with prior L-asparaginase therapy - Serious thrombosis with prior L-asparaginase therapy - Serious hemorrhagic events with prior L-asparaginase therapy | 4.3 Contraindications; - History of severe hypersensitivity to the active substance or to any of the excipients listed in section 6.1 - Current or past severe pancreatitis associated with L‑asparaginase therapy - Current pancreatitis not associated with L‑asparaginase therapy
Precautions | 5 WARNINGS AND PRECAUTIONS | 4.4 Special warnings and precautions for use; In order to improve traceability of biological medicinal products, the tradename and batch number of the administered product should be clearly recorded (or stated) in the patient file.
 | 5.1 Hypersensitivity Reactions; Grade 3 and 4 hypersensitivity reactions after the use of ERWINAZE have occurred in 5% of patients in clinical trials [see Adverse Reactions (6.1)]. | Hypersensitivity reactions; Administration of Erwinase can cause hypersensitivity reactions (infusion/injection reactions), including reactions presenting as anaphylaxis.; Severe reactions are common.; Reactions have occurred following the first or subsequent administrations.; There is little or no cross-reactivity between crisantaspase and E. coli-derived L-asparaginase.; Reactions include; - reactions limited to the area at or near the site of IM or IV administration, and - other reactions, including - reactions with symptoms consistent with an anaphylactic reaction, and - reactions accompanied by fever (see section 4.8).; Reactions can begin during or immediately following administration. In the majority of patients, local and non-local reactions occur within the first 24 hours. Later onset of reactions has been reported two days or later after IM administration.
 | Administer this product in a setting with resuscitation equipment and other agents necessary to treat anaphylaxis. If a serious hypersensitivity reaction occurs, discontinue ERWINAZE and initiate appropriate therapy. | Facilities should be made available for management of an anaphylactic reaction, should it occur, during administration. If a severe reaction occurs, Erwinase must be discontinued (see section 4.3).; Careful observation is required on re-exposure to L-asparaginase after any time interval (e.g. between induction and consolidation), which may increase the risk of anaphylactic and hypersensitivity reactions occurring.
 | 5.2 Pancreatitis; Pancreatitis has been reported in 4% of patients in clinical trials [see Adverse Reactions (6.1)].; Evaluate patients with symptoms compatible with pancreatitis to establish a diagnosis. Discontinue ERWINAZE for severe or hemorrhagic pancreatitis manifested by abdominal pain > 72 hours and amylase elevation ≥ 2.0 x ULN. Severe pancreatitis is a contraindication to additional asparaginase administration. In the case of mild pancreatitis, hold ERWINAZE until the signs and symptoms subside and amylase levels return to normal. After resolution, treatment with ERWINAZE may be resumed. | Pancreatitis; Treatment with L-asparaginase, including Erwinase, can cause pancreatitis. L-asparaginase-induced pancreatitis can be limited to biochemical and/or radiologic manifestations, progress to pancreatitis with clinical symptoms, and be severe (see section 4.8).; Fatal outcome of pancreatitis due to L-asparaginase products, including Erwinase, has been reported.; Patients must be closely monitored for signs and symptoms of pancreatic toxicity and instructed to promptly report potential symptoms of pancreatitis. If pancreatitis is suspected based on clinical symptoms, serum amylase and lipase should be determined. In patients treated with L-asparaginase, increases of serum amylase and lipase may be delayed, mild or absent.; Erwinase must be permanently discontinued in case of severe pancreatitis (see section 4.3). Hypertriglyceridemia, if marked, can contribute to the development of pancreatitis (see section 4.8).; There have been isolated reports of first onset of clinical pancreatitis and detection of pancreatic pseudocyst formation several months after the last administration of L-asparaginase. Patients must be monitored for late-occurring signs of pancreatitis.; Development of chronic pancreatitis as well as persistent pancreatic insufficiency (exocrine insufficiency with, e.g., malabsorption; persistent glucose intolerance/diabetes mellitus) has been reported with L- asparaginase treatment.
 | 5.3 Glucose Intolerance; Glucose intolerance has been reported in 5% of patients receiving ERWINAZE in clinical trials [see Adverse Reactions (6.1)]. In some cases, glucose intolerance may be irreversible. Monitor glucose levels in patients at baseline and periodically during treatment. Administer insulin therapy as necessary in patients with hyperglycemia. | Glucose Intolerance; Treatment with L-asparaginase, including Erwinase, can cause glucose intolerance and potentially severe hyperglycemia.; In some patients, ketoacidosis has been reported.; Patients must be monitored for developing hyperglycemia and potential complications.; Administration of insulin and possibly discontinuation of L‑asparaginase treatment may be necessary to manage hyperglycemia.
 | 5.4 Thrombosis and Hemorrhage; Serious thrombotic events, including sagittal sinus thrombosis and pulmonary embolism have been reported with both E. coli and Erwinia-derived L-asparaginase therapy. The following coagulation proteins were decreased in the majority of patients after a 2-week course of ERWINAZE by intramuscular administration: fibrinogen, protein C activity, protein S activity, and anti-thrombin III.; Discontinue ERWINAZE for a thrombotic or hemorrhagic event until symptoms resolve; after resolution, treatment with ERWINAZE may be resumed. | Coagulation Disorders; Administration of L-asparaginase, including Erwinase, leads to decreased synthesis of coagulant, anticoagulant, and fibrinolytic proteins, abnormal coagulation times, and clinical coagulation abnormalities that can cause serious thromboembolic and bleeding events (see section 4.8).; Routine clotting screening should be performed before treatment initiation and monitored during treatment. Preventive measures must be considered.; If significant symptomatic coagulopathy occurs in addition to other clinically indicated interventions withhold Erwinase treatment until resolved. Treatment may then continue according to protocol, if the benefit of continued administration is considered to outweigh the risk from re-exposure.
Adverse reactions | 6 ADVERSE REACTIONS; The following clinically significant adverse reactions are discussed in greater detail in other sections of the label:; - Hypersensitivity reactions [see Warnings and Precautions (5.1)] - Pancreatitis [see Warnings and Precautions (5.2)] - Glucose intolerance [see Warnings and Precautions (5.3)] - Thrombosis and hemorrhage [see Warnings and Precautions (5.4)] | 4.8 Undesirable effects; a. Summary of the safety profile; The two most frequent adverse reactions are:; • Hypersensitivity, including urticaria, fever, arthralgia angioedema, bronchospasm, hypotension or even anaphylactic shock. In case of severe systemic hypersensitivity reaction, treatment should be discontinued immediately and withdrawn.; • Coagulation abnormalities (e.g. thromboses), due to protein synthesis impairment, are the second most frequent class of adverse reactions. Thromboses of peripheral, pulmonary or central nervous system blood vessels have been reported, potentially fatal or with residual delayed affects dependent upon the location of the occlusion. Other risk factors contributing to coagulation abnormalities include the disease itself, concomitant steroid therapy and central venous catheters.; Undesirable effects are generally reversible.
 | 6.1 Clinical Trials Experience; Because clinical trials are conducted under controlled, but widely varying conditions, adverse reaction rates observed in clinical trials of ERWINAZE cannot be directly compared to rates in the clinical trials of other drugs and may not reflect the rates observed in practice.; The data presented below are based on information collected from Study 1, a single-arm, multi-center, open-label, safety and clinical pharmacology trial (intramuscular administration), the ERWINAZE Master Treatment Protocol (EMTP), an expanded access program (both intramuscular, intravenous, and other or unknown administration), and Study 2, a single-arm, multi-center, open-label, pharmacokinetic (PK) study trial of intravenous administration of ERWINAZE.; Study 1 enrolled 58 patients treated on National Cancer Institute (NCI)-sponsored cooperative group ALL protocols who were unable to continue to receive pegaspargase due to hypersensitivity reactions.; Patients received 6 doses of ERWINAZE 25,000 International Units/m^2 intramuscularly on a Monday, Wednesday, and Friday schedule as a replacement for each scheduled dose of pegaspargase remaining on their original treatment protocol. The Study 1 population included patients with a median age of 11 years (2 to 18 years); 59% were male, 78% were White, 10% were Black/African American, 5% were Asian, and 7% were other or unknown. A total of 35% were Hispanic or Latino. In Study 1, the number of ERWINAZE courses ranged from 1 to 9. In this study, 76% (44 of 58) completed all planned therapy.; Fourteen (24%) patients stopped therapy prior to completion; seven due to allergic reactions, five due to physician or patient choice, one due to disease progression, and one due to discontinuation during frontline protocol. All other chemotherapy was continued according to the patient’s prescribed treatment regimen [see Clinical Studies (14)].; Study 2 enrolled 30 patients [29 were being treated for ALL and one for lymphoblastic lymphoma (LBL)] following allergy to native E. coli asparaginase or pegaspargase. Patients received ERWINAZE 25,000 International Unit/m /dose, administered by intravenous infusion on a Monday, Wednesday, and Friday schedule (6 doses) as a replacement for doses remaining on their original treatment plan. The Study 2 population included patients with a median age of 7 years (1 to 17 years); 63% were male, 27% were Hispanic or Latino, 83% were White, 3% were Black/African American, 7% were Asian, and 7% were other (American Indian, Alaska Native or Indian) [see Clinical Studies (14)].; The EMTP trial enrolled 1368 patients with ALL or lymphoblastic lymphoma who received ERWINAZE after developing systemic hypersensitivity to an E. coli-derived asparaginase. Of these 1368 patients, safety data were received for 940 patients with a median age of 9 years (0 to 76 years), 63% were male, 91% with leukemia, 3% with lymphoma, and 6% with unknown disease information.; Patients received ERWINAZE according to several schedules, and treatment center specifications with doses that ranged from 20,000 to 25,000 International Units/m^2. The route of administration was intramuscular n=852, intravenous n=29, other or unknown n=59. In the EMTP trial, the planned number of doses of ERWINAZE ranged from 3 to 48 doses. Seventy-eight percent of patients (693 of 893) were able to receive all planned doses to complete their prescribed treatment regimen.; In Study 1 and Study 2, safety information was prospectively and systematically collected. In Study 1, all Grades of adverse events were reported for the following adverse events of special interest: allergy, pancreatitis, coagulopathy (hemorrhage, thrombosis or infarct), hyperbilirubinemia, hyperglycemia, hyperlipidemia, ketoacidosis, and CNS events (hemorrhage, thrombosis or infarction, and cerebral venous thrombosis) and only Grade 3 and 4 events were reported for other adverse events. In Study 2 all adverse events of all Grades were prospectively collected. In the EMTP trial, safety data were derived from case report forms that collected adverse event information. The forms specifically requested information on occurrence of allergic reactions, thrombotic events, hemorrhagic events, hepatobiliary disorders, pancreatic disorders, and hyperglycemia.; The most common adverse reactions (incidence 1% or greater) with ERWINAZE treatment are systemic hypersensitivity, hyperglycemia, transaminases abnormal, fever, pancreatitis, local reactions, vomiting, nausea, thrombosis, hyperbilirubinemia, abdominal pain/discomfort, and diarrhea.; The incidence of non-hematologic, non-infectious, adverse events (all Grades) in Study 1, Study 2, and the EMTP trial is provided in Table 1.; The incidence of Grade 3 or greater non-hematologic, non-infectious adverse reactions occurring with ERWINAZE in Study 1, Study 2 and EMTP trial is provided in Table 2. | b. Tabulated list of adverse reactions; The adverse reaction data presented in Table 1 have been identified from 3 clinical studies (100EUSA12, ALL07P2, and Erwinase Master Treatment Protocol [EMTP]) with Erwinase in 1028 patients (primarily pediatric patients), the majority having acute lymphoblastic leukemia, as well as post-marketing experience with Erwinase and other L‑asparaginase preparations in pediatric and adult patients.; Some of the adverse reactions listed below are known to be associated with multi-agent chemotherapeutic regimens (e.g., reactions resulting from bone marrow depression, and infections), and the contributory role of Erwinase is not clear. In individual cases of other adverse reactions, other medicinal products of the regimen may have contributed.; Frequency definitions: very common (≥1/10), common (≥1/100 to <1/10), uncommon (≥1/1000 to <1/100), rare (≥1/10000 to <1/1000) and very rare (<1/10000).When no valid estimate of the incidence rate for an adverse event from available data can be calculated, the frequency of such ADR has been classified as “Not known”.; Posterior reversible encephalopathy syndrome; In rare cases, a posterior reversible encephalopathy syndrome (PRES) has been observed during therapy with asparaginase-containing regimens.
 | 6.2 Immunogenicity; As with all therapeutic proteins, there is potential for immunogenicity. The detection of antibody formation is highly dependent on the sensitivity and specificity of the assay. Additionally, the observed incidence of antibody (including neutralizing antibody) positivity in an assay may be influenced by several factors including assay methodology, sample handling, timing of sample collection, concomitant medications, and underlying disease. For these reasons, comparison of the incidence of antibodies in other studies or to other asparaginase Erwinia chrysanthemi products may be misleading.; In a study with ERWINAZE treatment by intramuscular administration (Study 1), 6 of 56 (11%) patients treated with ERWINAZE developed antibodies to ERWINAZE. Of these 6 anti-drug antibody (ADA) positive patients, one experienced a hypersensitivity reaction during Study 1 (2%, 1 of 56). None of these 6 patients had neutralizing antibodies.; In a study with ERWINAZE treatment by intravenous administration (Study 2), 4 of 30 (13.3%) patients treated with ERWINAZE developed anti-ERWINAZE antibodies. Of these 4 patients who developed anti-ERWINAZE antibodies, 3 experienced hypersensitivity reactions (10%, 3 of 30) during the study. None of these 4 patients had neutralizing antibodies.; The presence of ADA to ERWINAZE is associated with a higher risk of hypersensitivity reactions in patients who received ERWINAZE through intravenous infusion compared to intramuscular administration of ERWINAZE. | Immunogenicity; As with most therapeutic proteins, patients may potentially develop anti-drug antibodies (ADA) to crisantaspase.; Immunogenicity assays are highly dependent on the sensitivity and specificity of the assay and may be influenced by several factors such as: assay methodology, sample handling, timing of sample collection, concomitant medications, and underlying disease. For these reasons, comparison of the incidence of antibodies to crisantaspase with the incidence of antibodies to other products may be misleading.; In a study with Erwinase treatment by IM administration (Study ALL07P2), 6 of 56 (11%) patients treated with Erwinase developed antibodies to crisantaspase. Of these 6 ADA positive patients, one experienced a hypersensitivity reaction (2%, 1 of 56). None of these 6 patients had neutralising antibodies.; In a study with Erwinase treatment by IV administration (Study 100EUSA12), 4 of 30 (13.3%) patients treated with Erwinase developed anti-crisantaspase antibodies. Of these 4 patients, 3 experienced hypersensitivity reactions (10%, 3 of 30). None of these 4 patients had neutralising antibodies; Neutralising antibodies; As with other L-asparaginase preparations, development of specific neutralising antibodies has been reported with repeated dosing and is associated with reduced L-asparaginase activity.; Reporting of suspected adverse reactions; Reporting suspected adverse reactions after authorisation of the medicinal product is important. It allows continued monitoring of the benefit/risk balance of the medicinal product. Healthcare professionals are asked to report any suspected adverse reactions via Yellow Card Scheme Website: www.mhra.gov.uk/yellowcard or search for MHRA Yellow Card in the Google Play or Apple App Store.
Drug interactions | Note: The following information is provided in the USPI under section 12.3 Pharmacokinetics; Drug Interaction Studies; No formal drug interaction studies between ERWINAZE and other drugs have been performed | 4.5 Interaction with other medicinal products and other forms of interaction; No formal medicinal product interaction studies have been performed.; Asparaginase must not be mixed with any other medicinal products prior to administration.; In addition concomitant use of L-asparaginase and medicinal products affecting liver function may increase the risk of a change in liver parameters (e.g. increase of ASAT, ALAT, bilirubin).; Since an indirect interaction between components of the oral contraception and asparaginase cannot be ruled out, oral contraceptives are not considered sufficiently safe in such clinical situation. Another method than oral contraception should be used in women of childbearing potential (see section 4.6).; • Methotrexate, cytarabine; L-asparaginase may diminish or abolish methotrexate’s and cytarabine’s effect on malignant cells; this effect persists as long as plasma asparagine levels are suppressed. Accordingly, do not use methotrexate or cytarabine with, or following L-asparaginase, while asparagine levels are below normal.; Alternatively, administration of L-asparaginase after methotrexate or cytarabine results in a synergistic effect. The extent to which these affect the overall effectiveness of established treatment protocols is not known.; • Prednisone; Concomitant use of prednisone and L-asparaginase may increase the risk of a change in clotting parameters (e.g. a decrease in fibrinogen and ATIII levels).; • Vincristine; Administration of vincristine concurrently with or immediately before treatment with L-asparaginase may be associated with increased toxicity and increased risk of anaphylaxis.
Special populations | 8 USE IN SPECIFIC POPULATIONS; 8.1 Pregnancy; Risk Summary; Based on findings from animal reproduction studies, ERWINAZE can cause fetal harm when administered to a pregnant woman. In animal reproduction studies, intramuscular administration of asparaginase Erwinia chrysanthemi to pregnant rats and rabbits during organogenesis at doses approximately 0.005-0.5 times the maximum recommended human dose resulted in structural abnormalities and embryo-fetal mortality (see Data). There are no available data on ERWINAZE use in pregnant women to evaluate the drug-associated risk of major birth defects, miscarriage or adverse maternal or fetal outcomes. Advise pregnant women of the potential risk to the fetus.; The estimated background risk of major birth defects and miscarriage for the indicated population is unknown. Adverse outcomes in pregnancy occur regardless of the health of the mother or the use of medications. In the U.S. general population, the estimated background risks of major birth defects and miscarriage in clinically recognized pregnancies are 2 to 4% and 15 to 20%, respectively. | 4.6 Fertility, pregnancy and lactation; Pregnancy; There are no adequate data from the use of crisantaspase (Erwinia L-asparaginase) in pregnant women. Limited reports in humans of the use of E. coli asparaginase in combination with other antineoplastics during pregnancy did not provide sufficient data to conclude. However, based on effects on embryonal/foetal development shown in pre-clinical studies (see section 5.3),; Erwinase should not be used during pregnancy unless the potential benefit justifies the potential risk to the fetus.
 | Data; Animal Data; In embryofetal development studies, asparaginase Erwinia chrysanthemi was administered intramuscularly every other day during the period of organogenesis to pregnant rats (at 3000, 6000, or 12000 IU/m^2) and rabbits (at 120, 300, or 480 IU/m^2). In rats given 12000 IU/m^2 (approximately 0.5 times the maximum recommended human dose), maternal toxicity of decreased body weight gain was observed, as well as a fetal finding of increased incidence of partially undescended thymic tissue.; In rabbits, maternal toxicity consisting of decreased body weight was observed at 480 IU/m^2 (approximately 0.02 times the maximum recommended human dose). Increased post-implantation loss, a decrease in the number of live fetuses, and gross abnormalities (e.g., absent kidney, absent accessory lung lobe, additional subclavian artery, and delayed ossification) were observed at doses of ≥120 IU/m^2 (approximately 0.005 times the maximum recommended human dose). | Fertility; There are no human data on the effect of crisantaspase on fertility. In rats, crisantaspase did not affect male and female fertility. However, a decrease in sperm count was observed in male rats (see section 5.3). The relevance of this finding to humans is not known.
 | 8.2 Lactation; Risk Summary; There are no data on the presence of asparaginase Erwinia chrysanthemi in human or animal milk, the effects on the breastfed child, or the effects on milk production. Because of the potential for serious adverse reactions in the breastfed child, advise patients that breastfeeding is not recommended during treatment with ERWINAZE, and for 3 months after the last dose. | Breast feeding; It is not known whether crisantaspase (Erwinia L-asparaginase) is excreted in human breast milk. Potential serious adverse reactions may occur in nursing infants, therefore Erwinase should be discontinued during breast-feeding.
 | 8.3 Females and Males of Reproductive Potential; Pregnancy Testing; Pregnancy testing is recommended for females of reproductive potential before starting ERWINAZE treatment.; Contraception; Females; ERWINAZE can cause embryo-fetal harm when administered to pregnant women [see Use in Specific Populations (8.1)]. Advise females of reproductive potential to use effective contraception during treatment with ERWINAZE and for 3 months after the final dose. Since an indirect interaction between oral contraceptives and ERWINAZE cannot be ruled out, a method of contraception other than oral contraceptives should be used in women of childbearing potential. | Women of childbearing potential/Contraception in males and females; Women of childbearing potential should use effective contraception and avoid becoming pregnant while being treated with asparaginase-containing chemotherapy.; Since an indirect interaction between components of the oral contraception and asparaginase cannot be ruled out, oral contraceptives are not considered sufficiently safe in such clinical situation. A method other than oral contraceptives should be used in women of childbearing potential.; Men should use effective contraceptive measures and be advised to not father a child while receiving asparaginase.; The time period following treatment with asparaginase when it is safe to become pregnant or father a child is unknown. As a precautionary measure it is recommended to wait for three months after completion of treatment. However, treatment with other chemotherapeutic agents should also be taken into consideration.
 | 8.4 Pediatric Use; The safety and effectiveness of ERWINAZE have been established in pediatric patients ages1 year and older as a component of a multi-agent chemotherapeutic regimen for the treatment of patients with acute lymphoblastic leukemia (ALL) who have developed hypersensitivity to E. coli-derived asparaginase and the information on this use is discussed throughout the labeling. | d. Pediatric population; Compared with children, the incidence of hepatic and pancreatic toxicities and of venous thromboembolic events may be increased in adolescents and young adults.
 | 8.5 Geriatric Use; Clinical studies of ERWINAZE did not include geriatric patients. | e. Other special populations; No special individual populations of patients have been identified in which the safety profile differs from that defined above.
Overdosage | There are no corresponding clinical data for Erwinaze USPI | 4.9 Overdose; There is no known antidote for asparaginase overdoses. No data are available on the elimination (peritoneal or by haemodialysis) of the product. Patients who accidentally receive an overdose of L-asparaginase should be monitored closely and receive any appropriate symptomatic and supportive treatment.
 | 12 CLINICAL PHARMACOLOGY | 5. PHARMACOLOGICAL PROPERTIES; 5.1 Pharmacodynamic properties; Pharmacotherapeutic group: other antineoplastic agents ATC code: L01XX02
 | 12.1 Mechanism of Action; Asparaginase Erwinia chrysanthemi catalyzes the deamidation of asparagine to aspartic acid and ammonia, resulting in a reduction in circulating levels of asparagine. The mechanism of action of ERWINAZE is thought to be based on the inability of leukemic cells to synthesize asparagine due to lack of asparagine synthetase activity, resulting in cytotoxicity specific for leukemic cells that depend on an exogenous source of amino acid asparagine for their protein metabolism and survival. | Mechanism of action; L-asparaginase catalyses the deamination of asparagine to aspartic acid with the release of ammonia.; Asparagine is an amino acid found incorporated into most proteins, and protein synthesis is halted in its absence, thereby inhibiting RNA and DNA synthesis with a resulting halt to cellular proliferation.; As lymphoblastic cells are lacking asparagine synthetase activity they are dependent upon exogenous asparagine. The anti-tumour activity of L-asparaginase is a result of the sustained depletion of exogenous asparagine.; It has also been noted that asparaginase, in addition to its asparaginase activity, has significant glutaminase activity. It catalyses the deamination of glutamine in glutamic acid with the release of ammonia.; Glutamine may lead to alternative asparagine synthesis and therefore glutamine depletion may complement asparagine depletion. However, exact potential of this glutaminase activity remains unknown.
 | 12.3 Pharmacokinetics; Based on a population PK model, the mean (%CV) half-life of intravenous ERWINAZE was 7.51 (23.9%) hours in contrast to a mean (%CV) half-life of 15.6 (20%) hours reported for intramuscular ERWINAZE. These differences in PK between intravenous and intramuscular ERWINAZE are reflected in the proportion of patients with 2-day and 3-day nadir serum asparaginase activity (NSAA) levels of asparaginase Erwinia chrysanthemi ≥ 0.1 or 0.4 IU/mL [see Clinical Studies (14)].; Following administration of ERWINAZE 25,000 International Units/m^2 intramuscularly to 48 ALL patients aged ≥ 2 years to ≤ 18 years in Study 1 on a Monday, Wednesday, and Friday schedule for 6 doses, 100% of patients who completed Course 1 achieved NSAA levels ≥ 0.1 International Units/mL at either 48 hours (n=35) or 72 hours (n=13) post dose 3. Eighty percent (28/35) of those evaluated at 48 hours and 38% (5/13) evaluated at 72 hours had nadir serum asparaginase activity levels ≥ 0.4 International Units/mL [see Clinical Studies (14)].; Following intravenous administration of ERWINAZE 25,000 International Units/m^2 to 24 evaluable patients (aged ≥ 1 year to ≤ 17 years) in Study 2 on a Monday, Wednesday, and Friday schedule, 83% (20/24) and 43% (9/21) of patients who completed Course 1 achieved NSAA levels ≥ 0.1 International Units/mL at 48 hours post-dose 5 and 72 hours post dose 6, respectively. Twenty-nine percent (7/24) of those evaluated at 48 hours and no patients (0/21) evaluated at 72 hours had nadir serum asparaginase activity levels ≥ 0.4 International Units/mL [see Clinical Studies (14)].; Drug Interaction Studies; No formal drug interaction studies between ERWINAZE and other drugs have been performed | 5.2 Pharmacokinetic properties; Based on a population PK model, the mean (%CV) half-life of crisantaspase is 7.5 (24%) hours after intravenous infusion in contrast to 15.6 (20%) hours after intramuscular injection. L-asparaginase penetrates through to the cerebrospinal fluid to a small degree and is also found in lymph.; Serum trough asparaginase activity ≥ 0.1 U/mL has been demonstrated to correlate with asparagine depletion (asparagine < 0.4 mcg/mL or 3 μM) and to serum levels that predict clinical efficacy.; Clinical trials; Study 1 (AALL07P2) was a single-arm, multicentre, open-label, safety and clinical pharmacology trial, which enrolled ALL patients who were unable to continue to receive pegaspargase due to hypersensitivity reactions. The main outcome measure was the proportion of patients who achieved a serum trough asparaginase level ≥ 0.1 IU/mL, which correlates with asparagine depletion and predicts clinical efficacy. Patients received Erwinase 25,000 IU/m^2 intramuscularly for two weeks (total 6 doses) as a replacement for each scheduled dose of pegaspargase.; Out of 58 patients enrolled, 48 were evaluable for the main outcome measure in the first treatment course. The median age was 11 years (2 to 18 years) and 59% were male.; Study 2 (100EUSA12) was a single-arm, multicentre pharmacokinetic study in patients with ALL/LBL who had developed hypersensitivity to native E. coli asparaginase, pegaspargase, or calaspargase pegol. Patients received Erwinase 25,000 IU/m^2 intravenously 3 days per week for up to 30 weeks. The main outcome measure was the proportion of patients with 2-day nadir serum asparaginase activity (NSAA) levels after the fifth dose ≥ 0.1 IU/mL.; Out of 30 patients enrolled, 24 were evaluable for the main outcome measure in the first treatment course. The median age was 7 years (1-17 years) and 63% were male.; The results of the two studies are presented in the table below.; Proportion of patients with sustained asparaginase activity; Neutralising antibodies; As with other L-asparaginase preparations, development of specific neutralising antibodies has been reported with repeated dosing and is associated with reduced L-asparaginase activity.; Cerebrospinal fluid activity; After IM administration of 25,000 IU/m^2 Erwinase per week for 16 weeks, CSF L-asparagine levels were undetectable 3 days after last administration in 5 of 8 children (62.5%), and in 2 of 8 children (25%) after both the 5th and 6th administration during reinforced re-induction therapy.
Carcinogenesis, Mutagenesis, Impairment of Fertility | 13 NONCLINICAL TOXICOLOGY; 13.1 Carcinogenesis, Mutagenesis, Impairment of Fertility; No long-term carcinogenicity studies in animals have been performed with asparaginase Erwinia chrysanthemi. No studies that assess the mutagenic potential of asparaginase Erwinia chrysanthemi have been conducted.; In a fertility and early embryonic development study in rats, asparaginase Erwinia chrysanthemi had no effect on male or female fertility when administered intramuscularly at doses of up to 12000 IU/m^2 (approximately 0.50 times the maximum recommended human dose) every other day for a total of 35 doses. Findings in males included decreased sperm count at doses of more than 3000 IU/m^2 (approximately 0.12 times the maximum recommended human dose). | 5.3 Preclinical safety data; Adverse reactions not observed in clinical studies, but seen in animals at exposure levels similar to clinical exposure levels and with possible relevance to clinical use were as follows:; Reproduction and development toxicity; Embryotoxicity studies with Erwinia L-asparaginase have given evidence of teratogenic potential in rabbits. In addition, pre-clinical experience with other asparaginase preparations has shown teratogenic potential in rats, mice and rabbits with doses in the therapeutic ranges.; In a fertility and early embryonic development study in rats, IM administration of crisantaspase had no effect on male and female fertility at doses approximately 50% of the recommended human dose (based on body surface area). However, a 12 to 15% decrease in sperm count was observed at doses approximately 12 to 50% of the recommended human dose.; Carcinogenicity; Non-clinical studies have not been conducted to evaluate the carcinogenic or mutagenic potential of crisantaspase. Crisantaspase is an enzyme for which the structure and well documented activity do not suggest any carcinogenic or mutagenic potential.
Clinical data | 14 CLINICAL STUDIES; The efficacy of ERWINAZE for the treatment of patients with acute lymphoblastic leukemia (ALL) who have developed hypersensitivity to E. Coli-derived asparaginase as a component of a multi-agent chemotherapeutic regimen was established in Study 1, a single-arm, multi-center, open-label, safety and clinical pharmacology trial. Additional safety data were obtained in the ERWINAZE Master Treatment Protocol (EMTP), an expanded access program [see Adverse Reactions (6)]. Study 1 enrolled patients treated on National Cancer Institute (NCI)-sponsored cooperative group ALL protocols who were unable to continue to receive pegaspargase due to hypersensitivity reactions. The main outcome measure was determination of the proportion of patients who achieved a serum trough asparaginase level greater than or equal to 0.1 International Units/mL. Serum trough asparaginase activity ≥ 0.1 International Units/mL has been demonstrated to correlate with asparagine depletion (asparagine < 0.4 mcg/mL or 3 μM) and to serum levels that predict clinical efficacy. Patients received ERWINAZE 25,000 International Units/m^2 intramuscularly for two weeks (total 6 doses) as a replacement for each scheduled dose of pegaspargase remaining on their original treatment protocol.; Fifty-eight patients were enrolled in Study 1, of these 48 were evaluable for the main outcome measure based on availability of pharmacokinetic samples in Course 1. The median age was 11 years (2 to 18 years); 59% were male, 78% were White, 10% were Black/African American, 5% were Asian, and 7% were other or unknown. A total of 35% were Hispanic or Latino.; Study 1 met its main outcome measure of demonstrating that greater than 50% of the patients achieved the pre-specified trough asparaginase activity level of ≥ 0.1 International Units/mL at 48 or 72 hours following the third dose. Results for the main outcome measure and for an exploratory analysis using a higher cut-off (trough serum asparaginase activity levels ≥ 0.4 International Units/mL are presented in Table 3 [see Clinical Pharmacology (12.3)].; The safety and efficacy of intravenous administration were determined in Study 2 by characterizing the PK of a 25,000 International Units/m^2 ERWINAZE dose given 3 days per week on a Monday, Wednesday, and Friday schedule for up to 30 weeks. This open-label, single-arm, multicenter PK study enrolled 30 patients. The main outcome measure was determination of the proportion of patients with 2-day NSAA levels (48-hour levels taken after the fifth dose) ≥ 0.1 International Unit/mL in the first 2 weeks of ERWINAZE treatment.; Of the thirty patients enrolled, 24 were evaluable for the main outcome measure based on the pharmacokinetic samples in Course 1. The median age was 7 years (1-17 years), 63% were male, 27% were Hispanic or Latino, 83% were White, 3% were Black/African American, 7% were Asian, and 7% were other (American Indian, Alaska Native, or Indian).; In Study 2, serum asparaginase activity of asparaginase Erwinia chrysanthemi was determined in 24 evaluable patients (aged ≥ 1 year to ≤17 years) following intravenous administration of ERWINAZE 25,000 International Units/m^2. Five minutes after the 60-minute infusion in Course 1, the mean asparaginase activity level was 12.65 ± 3.16 International Unit/mL post-dose 1 and 12.11 ± 3.11 International Unit/mL post dose 4. The main study objective was met with an asparaginase activity level of ≥ 0.1 International Units/mL 48 hours after the fifth dose observed in 83% of patients. The 72-hour post dose 6 asparaginase activity level of ≥ 0.1 International Unit/mL was the secondary endpoint, with 43% of patients achieving this endpoint. Results are presented in Table 3 [see Clinical Pharmacology (12.3)]. | 5.2 Pharmacokinetic properties; Based on a population PK model, the mean (%CV) half-life of crisantaspase is 7.5 (24%) hours after intravenous infusion in contrast to 15.6 (20%) hours after intramuscular injection. L-asparaginase penetrates through to the cerebrospinal fluid to a small degree and is also found in lymph.; Serum trough asparaginase activity ≥ 0.1 U/mL has been demonstrated to correlate with asparagine depletion (asparagine < 0.4 mcg/mL or 3 μM) and to serum levels that predict clinical efficacy.; Clinical trials; Study 1 (AALL07P2) was a single-arm, multicentre, open-label, safety and clinical pharmacology trial, which enrolled ALL patients who were unable to continue to receive pegaspargase due to hypersensitivity reactions. The main outcome measure was the proportion of patients who achieved a serum trough asparaginase level ≥ 0.1 IU/mL, which correlates with asparagine depletion and predicts clinical efficacy. Patients received Erwinase 25,000 IU/m^2 intramuscularly for two weeks (total 6 doses) as a replacement for each scheduled dose of pegaspargase.; Out of 58 patients enrolled, 48 were evaluable for the main outcome measure in the first treatment course. The median age was 11 years (2 to 18 years) and 59% were male.; Study 2 (100EUSA12) was a single-arm, multicentre pharmacokinetic study in patients with ALL/LBL who had developed hypersensitivity to native E. coli asparaginase, pegaspargase, or calaspargase pegol. Patients received Erwinase 25,000 IU/m^2 intravenously 3 days per week for up to 30 weeks. The main outcome measure was the proportion of patients with 2-day nadir serum asparaginase activity (NSAA) levels after the fifth dose ≥ 0.1 IU/mL.; Out of 30 patients enrolled, 24 were evaluable for the main outcome measure in the first treatment course. The median age was 7 years (1-17 years) and 63% were male.; The results of the two studies are presented in the table below.; Proportion of patients with sustained asparaginase activity; Cerebrospinal fluid activity; After IM administration of 25,000 IU/m^2 Erwinase per week for 16 weeks, CSF L-asparagine levels were undetectable 3 days after last administration in 5 of 8 children (62.5%), and in 2 of 8 children (25%) after both the 5th and 6th administration during reinforced re-induction therapy.
Supply, storage and handling | 16 HOW SUPPLIED/STORAGE AND HANDLING; ERWINAZE is a sterile, white lyophilized powder supplied in a clear 3 mL glass vial. Each carton of ERWINAZE (NDC 57902-249-05) contains 5 vials. Each single vial (NDC 57902-249-01) contains 10,000 International Units asparaginase Erwinia chrysanthemi.; Store unused or unopened vials and cartons at 36°F to 46°F (2°C to 8°C). Protect from light. Do not use ERWINAZE after the expiration date on the vial. | 6.5 Nature and contents of container; Type 1 clear neutral glass vials of 3 ml nominal capacity, closed with 13 mm halobutyl freeze-drying stoppers and aluminium overseals, containing a white lyophilised solid.; Pack size: 5 vials.; 6.4 Special precautions for storage; Store in a refrigerator (+2°C to +8°C).; For storage conditions of the reconstituted medicinal product, see section 6.3.
 | 17 PATIENT COUNSELING INFORMATION; Hypersensitivity; Inform patients of the risk of allergic reactions, including anaphylaxis. Instruct patients on the symptoms of allergic reactions and to seek medical advice immediately if they experience such symptoms [see Warnings and Precautions (5.1)].; Pancreatitis; Instruct patients on the risk of pancreatitis and to seek medical advice immediately if they experience abdominal pain [see Warnings and Precautions (5.2)].; Glucose Intolerance; Instruct patients on the risk of hyperglycemia and glucose intolerance. Advise patients to seek medical advice if they experience excessive thirst or any increase in the volume or frequency of urination [see Warnings and Precautions (5.3)].; Thrombosis; Instruct patients on the risk of thrombosis and hemorrhage and to seek medical advice immediately if they experience headache, arm or leg swelling, shortness of breath, and chest pain [see Warnings and Precautions (5.4)].; Pregnancy and Lactation; Advise female patients of reproductive potential to use effective contraceptive methods while receiving ERWINAZE and for at least 3 months after the last dose. Advise patients to notify their healthcare provider immediately in the event of a pregnancy or if pregnancy is suspected during ERWINAZE treatment [see Use in Specific Populations (8.3)]. Advise lactating women not to breastfeed during treatment with ERWINAZE and for at least 3 months after the last dose [see Use in Specific Populations (8.2)]. | There is no corresponding section for Erwinase SmPC
Company information | Manufactured by:; Jazz Pharmaceuticals, Inc.; 3170 Porter Drive, Palo Alto, CA 94304; U.S. License No. 1901; Erwinaze® is a registered trademark of Porton Biopharma Limited used under license by Jazz Pharmaceuticals.; PRINCIPAL DISPLAY PANEL; 5 Vials NDC 57902-249-05; asparaginase Erwinia chrysanthemi Erwinaze®; For injection, Intramuscular or Intravenous Use; 10,000 International Units per Vial; Rx Only Single Dose Vial. Discard unused portion. | 7. MARKETING AUTHORISATION HOLDER; Porton Biopharma Limited Manor Farm Road; Porton Down, Salisbury, SP4 0JG United Kingdom; 8. MARKETING AUTHORISATION NUMBER(S); PL 44403/0002; 9. DATE OF FIRST AUTHORISATION/RENEWAL OF THE AUTHORISATION; First authorisation: 19 July 1985; Latest renewal: 25 May 2006; 10. DATE OF REVISION OF THE TEXT; 06/2020

PATIENT INFORMATION

Erwinase U.K. Package Leaflet, Information for the Patient

Package leaflet: Information for the patient Erwinase

10,000 IU, Powder for solution for injection/infusion Crisantaspase (L-asparaginase from Erwinia chrysanthemi)

Read all of this leaflet carefully before you start receiving this medicine because it contains important information for you.

- Keep this leaflet. You may need to read it again.
- If you have any further questions, ask your doctor or your pharmacist.
- If you get any side effects, talk to your doctor or pharmacist or nurse. This includes any possible side effects not listed in this leaflet. See section 4.

What is in this leaflet

1. What Erwinase is and what it is used for
2. What you need to know before you are given Erwinase.
3. How Erwinase is given
4. Possible side effects
5. How to store Erwinase
6. Contents of pack and other information

1. What Erwinase is and what it is used for

How does Erwinase work

Erwinase is an anti-blood-cell-cancer treatment from the pharmacotherapeutic group: Antineoplastic and immunomodulating agents. It works by lowering the levels of asparagine in your body, a substance the cancer cells need to survive.

What this medicine is used for

Erwinase is used for the treatment of a cancer of the white blood cells called Acute Lymphoblastic Leukaemia, in patients aged 4 months and above, who have developed allergic reactions to E.coli derived asparaginase.

Erwinase may be used alone or with other treatments.

2. What you need to know before you are given Erwinase

You should not be given Erwinase if:

■ you have previously had a severe allergic reaction to the active substance (Crisantapase- L- asparaginase from Erwinia chrysanthemi) or are allergic to any of the other ingredients of this medicine (see section 6).

■ You have, or have previously, had serious problems with your pancreas (severe pancreatitis) from using a medicine containing L-asparaginase

■ You have serious problems with your pancreas (severe pancreatitis)

Warnings and precautions

Talk to your doctor or pharmacist or nurse before taking Erwinase.

The following complications may arise during treatment with Erwinase:

- Serious life threatening allergic reactions. The hospital will have the necessary precautions in place to deal with such situations.
- Inflammation of the pancreas. If you experience abdominal pain this may be a sign of pancreatitis and should be reported to your doctor immediately. Fatal outcomes associated with pancreatitis have occurred.
- Increases in your blood sugar levels (Hyperglycemia). This can be controlled by receiving insulin sometimes even to fatal amounts (Hyperglycemia). This can be controlled by receiving insulin.
- Bleeding and blood clot disorders. During treatment your body’s ability to prevent excessive bleeding may be affected. In the case you experience any significant bleeding your treatment will be stopped. Your doctor will determine if, and when, treatment can be restarted.
- Liver dysfunctions can be caused or worsened. Discontinuation of Erwinase will be considered in the event of a severe reaction. Treatment can be restarted under close monitoring, but only once at least near complete recovery is achieved.
- Neurological disorders have been reported with fatal outcomes. Posterior reversible encephalopathy syndrome (characterised by headache, confusion, seizures and visual loss) may require blood- pressure lowering medicines and in case of seizure, anti-epileptic treatment.
- Kidney impairment due to high levels of a substance called uric acid in your blood from the chemotherapy.
- Reduced immune system that may increase your chances of an infection.

Monitoring during treatment with Erwinase

You will be monitored closely during and after treatment with Erwinase for:

- Allergic reactions
- Pancreas, kidney and liver functions
- Normal blood content

For traceability purposes your health care professional will record the product name and batch number for each dose of Erwinase you receive.

Other medicines and Erwinase

Tell your doctor or your pharmacist if you are taking or have recently taken any other medicines, including medicines obtained without a prescription, particularly any of the following:

- Types of medicines used to treat cancer called ‘methotrexate’ or ‘cytarabine’ as they can affect the way Erwinase works.
- Prednisone which is used in cancer treatment may increase the risk of a change in clotting.
- Vincristine which is used in cancer treatment, this can increase the toxic effects of both medicinal products and increase the risk of anaphylaxis.
- Oral contraceptives.

Your doctor or your nurse will not mix Erwinase with other medicines in the same infusion.

However you will probably be given other medicines before, during or after Erwinase treatment as part of your course of therapy.

Pregnancy

If you are pregnant, think you may be pregnant, or are planning to have a baby, ask your doctor or pharmacist for advice before taking this medicine.

Breastfeeding

You must not breast-feed your baby during your treatment with Erwinase, there may be a risk to the feeding child.

Fertility & Family planning

Potential for a decrease in male fertility cannot be out ruled.

When appropriate both men and women should use necessary contraceptive measures before, and for at least three months after treatment with Erwinase. Women should use a form of contraception other than oral contraceptives.

Driving and using machines

Erwinase can cause dizziness and drowsiness. This can affect your coordination and therefore your ability to drive and operate machinery.

Erwinase contains sodium and glucose

Erwinase contains the following ingredients:

■ sodium (less than 23 mg per dose). You can consider this medicine as essentially sodium free if you are on a salt-free or low-salt diet.

■ glucose. If you are diabetic, please note that each bottle of Erwinase contains 5 mg glucose.

3. How Erwinase is given

Dosage

Erwinase will only be given to you by health care professionals who are experienced in giving chemotherapy.

Your doctor will decide what dose to administer, how often you will be given Erwinase and for how long. It varies according to your body weight, your specific condition being treated, and your response to therapy.

Method of administration

Erwinase can be given to you in one of the following ways:

a) Into a vein (intravenous use). This may be given over 1 to 2 hours.

b) Into a muscle (intramuscular use).

If you are given more Erwinase than you should

If you are concerned that you have been given too much Erwinase, contact your doctor or another healthcare professional immediately.

If you think you have missed a dose of Erwinase

If you are concerned that you have missed a dose, contact your doctor or another healthcare professional immediately.

If you have any further questions on this product, ask your doctor, pharmacist or nurse.

4. Possible side effects

Like all medicines, Erwinase can cause side effects, although not everybody gets them. Erwinase will be given under strict medical supervision and your doctor may give you other medicines to treat these side effects. Most of the side effects will stop once you stop taking Erwinase.

Serious side effects

Tell your doctor immediately if you experience:

- Severe allergic reactions including blue discolouration of the lips and extremities (possible symptoms of hypoxia), swelling of the face and/or, shortness of breath, increased heart rate; wheezing, difficulty swallowing, hay fever like symptoms, rash, chills, flushing, high or low blood pressure, vomiting
- Redness, pain, swelling, bruising, or hardening of the skin at the site of the injection
- Damage to the Central Nervous System symptoms may include coma, encephalopathy, hallucinations, muscle weakness, confusion, dizziness, drowsiness, agitation, difficulty speaking
- Arm, leg or calf pain with or without swelling (symptoms of blood clots in the arm or leg), abdominal pain (symptoms of a blood clot in the area of the stomach, intestines, and kidneys) chest pain spreading to the arms, neck, jaw, back or stomach, feeling sweaty and breathless (which may be symptoms of a heart attack/myocardial infarction)
- Pain near your stomach or in your back (this may be inflammation of your pancreas)
- High blood sugar levels (hyperglycemia)
- Increased frequency of bleeding events including bruising even if you have not been injured
- Changes in liver functions (identified by laboratory testing)

Other side effects

Talk to your doctor if you get any of the following:

Very common side effects (may affect more than 1 in 10 people):

- Infections, including blood infections caused by bacteria (sepsis). This may be due to low levels of white cells in your blood. You may experience fever, a rapid heart rate, confusion or a rash.
- Decreases in normal blood content. Some of which may be due to reduced bone marrow activity.
- Increase in blood fats, bilirubin, creatinine, urea levels and certain liver enzymes- your doctor will monitor these.
- Weight loss
- Generalised pain/Muscle pains
- Nausea

Common (may affect up to 1 in 10 people) side effects include:

- Difficulty breathing or stopping breathing
- Mucositis (inflammation of the digestive tract)
- Diarrhoea
- Abdominal pain/discomfort
- tiredness or headache
- High temperature

Uncommon (may affect up to 1 in 100 people) side effects include:

- life threatening complications of uncontrolled diabetes
- High blood levels of ammonia
- Fits (convulsions)
- Build up of fats in the liver
- Kidney dysfunction

Rare (may affect up to 1 in 1,000 people) side effects include:

- Posterior reversible encephalopathy syndrome (a condition characterised by headache, confusion, seizures and visual loss).

Not known (frequency cannot be estimated from the available data)

- Inflammation of the salivary gland at the back of the throat
- Liver failure, increased mass of liver, jaundice
- Decreased albumin levels in the blood causing water retention
- Blistering and peeling of the skin (Toxic epidermal necrolysis)
- Joint pain

Additional side effects in children and adolescents

Liver, pancreas and blood clotting side effects may be higher in adults compared to children.

Reporting of side effects

If you get any side effects, talk to your doctor or,pharmacist. This includes any possible side effects not listed in this leaflet. You can also report side effects directly via MHRA Yellow Card in Google Play or Apple App Store.

By reporting side effects you can help provide more information on the safety of this medicine.

5. How to store Erwinase

Keep this medicine out of the sight and reach of children.

Erwinase will not be used after the expiry date printed on the label after “EXP”. The expiry date refers to the last day of the month.

The unopened Erwinase vials will be stored in a refrigerator (between +2°C to +8°C) by the hospital.

After reconstitution, the product should be used within 15 minutes. If the delay is more than 15 minutes, the solution should be withdrawn into a glass or polypropylene syringe and used within 8 hours. The reconstituted product should be stored below 25°C.

6. Contents of the pack and other information

What Erwinase contains

The active substance is crisantaspase (L-asparaginase from Erwinia chrysanthemi). Each vial contains 10,000 International units of cristanaspase (L-asparaginase from Erwinia chrysanthemi).

The other excipients are sodium chloride (See section 2) and glucose monohydrate (See section 2).

What Erwinase looks like and contents of the pack

Erwinase is provided as a powder for solution for injection/infusion

It comes as a white lyophilized powder in a clear glass bottle with a rubber stopper and an aluminium seal. Each pack contains 5 glass bottles of powder.

Marketing Authorisation Holder and Manufacturer

Porton Biopharma Limited, Manor Farm Road,

Porton Down, Salisbury, SP4 0JG United Kingdom

This leaflet was last revised in June 2020

Erwinase is a registered trademark of Porton Biopharma Limited.

PRINCIPAL DISPLAY PANEL

Erwinase Carton

Erwinase Vial